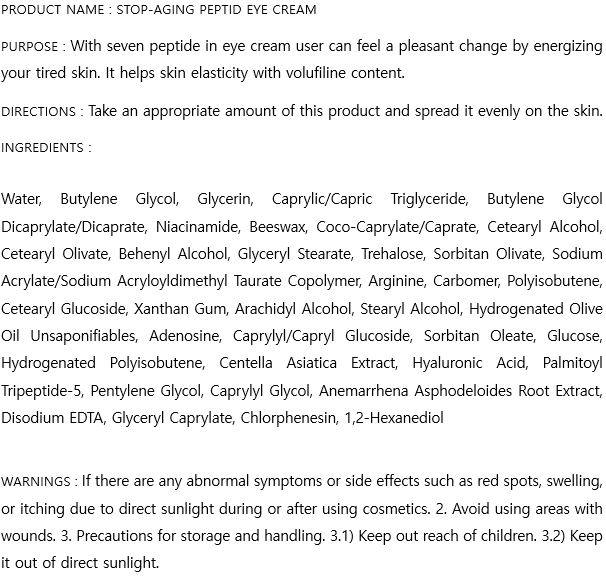 DRUG LABEL: STOP-AGING PEPTIDE EYE
NDC: 74997-0004 | Form: CREAM
Manufacturer: J&J COMPANY
Category: otc | Type: HUMAN OTC DRUG LABEL
Date: 20200810

ACTIVE INGREDIENTS: NIACINAMIDE 2 g/100 mL; ADENOSINE 0.04 g/100 mL
INACTIVE INGREDIENTS: GLYCERIN; BUTYLENE GLYCOL; WATER

J&J COMPANY - STOP-AGING PEPTIDE EYE CREAM

ACTIVE INGREDIENT

Niacinamide, Adenosine

INACTIVE INGREDIENT

Water, Butylene Glycol, Glycerin, Caprylic/Capric Triglyceride, Butylene Glycol Dicaprylate/Dicaprate, Niacinamide, Beeswax, Coco-Caprylate/Caprate, Cetearyl Alcohol, Cetearyl Olivate, Behenyl Alcohol, Glyceryl Stearate, Trehalose, Sorbitan Olivate, Sodium Acrylate/Sodium Acryloyldimethyl Taurate Copolymer, Arginine, Carbomer, Polyisobutene, Cetearyl Glucoside, Xanthan Gum, Arachidyl Alcohol, Stearyl Alcohol, Hydrogenated Olive Oil Unsaponifiables, Adenosine, Caprylyl/Capryl Glucoside, Sorbitan Oleate, Glucose, Hydrogenated Polyisobutene, Centella Asiatica Extract, Hyaluronic Acid, Palmitoyl Tripeptide-5, Pentylene Glycol, Caprylyl Glycol, Anemarrhena Asphodeloides Root Extract, Disodium EDTA, Glyceryl Caprylate, Chlorphenesin, 1,2-Hexanediol

PURPOSE

With seven peptide in eye cream user can feel a pleasant change by energizing your tired skin. It helps skin elasticity with volufiline content.

keep out of reach of the children

INDICATIONS AND USAGE

Take an appropriate amount of this product and spread it evenly on the skin.

WARNINGS

If there are any abnormal symptoms or side effects such as red spots, swelling, or itching due to direct sunlight during or after using cosmetics. 2. Avoid using areas with wounds. 3. Precautions for storage and handling. 3.1) Keep out reach of children. 3.2) Keep it out of direct sunlight.

DOSAGE AND ADMINISTRATION

for external use only